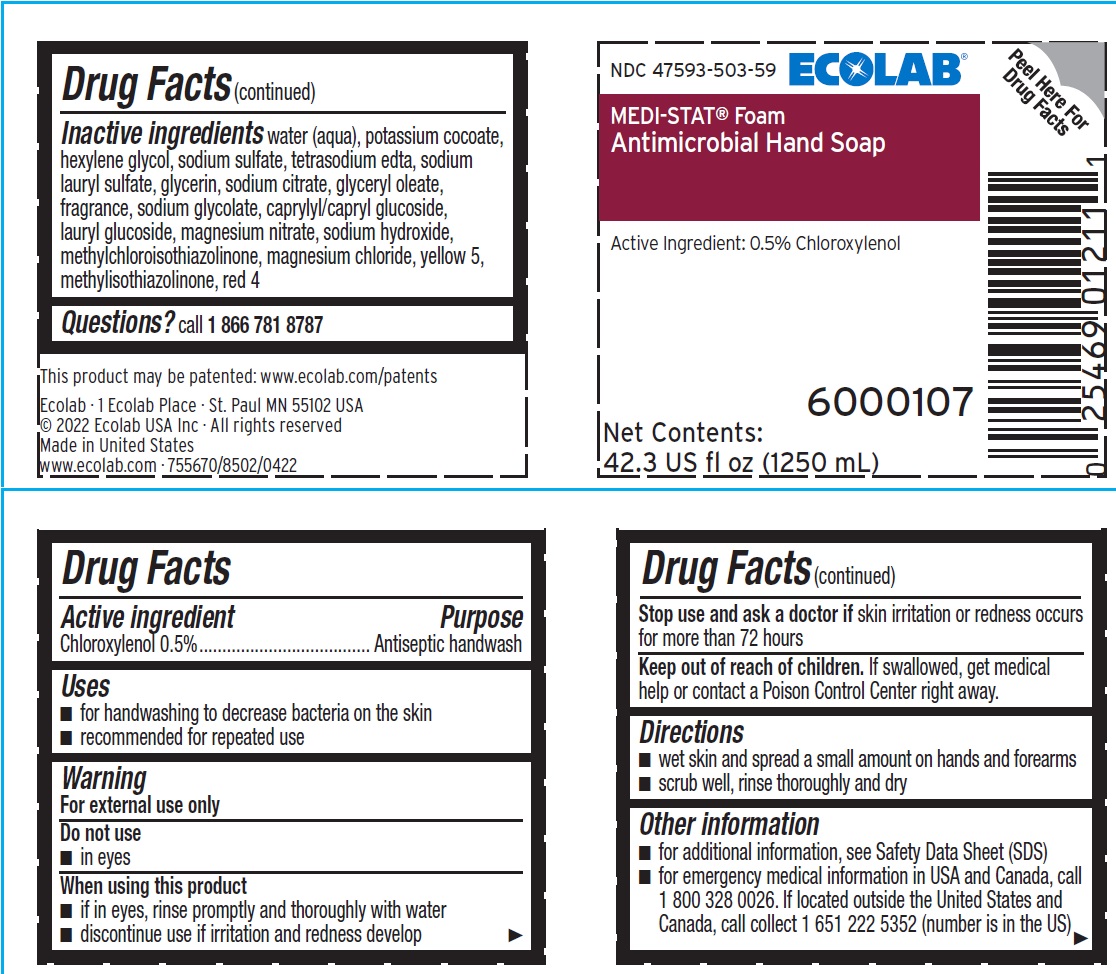 DRUG LABEL: Ecolab Inc.
NDC: 47593-503 | Form: LIQUID
Manufacturer: Ecolab Inc.
Category: otc | Type: HUMAN OTC DRUG LABEL
Date: 20240711

ACTIVE INGREDIENTS: CHLOROXYLENOL 5 mg/1 mL
INACTIVE INGREDIENTS: WATER; POTASSIUM COCOATE; HEXYLENE GLYCOL; SODIUM SULFATE; EDETATE SODIUM; SODIUM LAURYL SULFATE; GLYCERIN; SODIUM CITRATE; GLYCERYL OLEATE; SODIUM GLYCOLATE; DECYL GLUCOSIDE; LAURYL GLUCOSIDE; MAGNESIUM NITRATE; SODIUM HYDROXIDE; METHYLCHLOROISOTHIAZOLINONE; MAGNESIUM CHLORIDE; FD&C YELLOW NO. 5; METHYLISOTHIAZOLINONE; FD&C RED NO. 4

Drug Facts

Active ingredient

Chloroxylenol 0.5%

Purpose

Antiseptic handwash

Uses

- For handwashing to decrease bacteria on the skin
- Recommended for repeated use

Warnings

For external use only

Do not use

- In eyes

When using this product

- If in eyes, rinse promptly and thoroughly with water
- Discontinue use if irritation and redness develop

Stop use and ask a doctor if

- skin irritation or redness occurs for more than 72 hours

Keep out of reach of children. If swallowed, get medical help or contact a Poison Control Center right away.

Directions

- wet skin and spread a small amount on hands and forearms
- scrub well, rinse thoroughly and dry

Other information

- for additional infomration see Safety Data Sheet (SDS)
- for emergency medical information in USA and Canada, call 1 800 328 0026. If located outside the United States and Canada, call collect 1 651 222 5352 (number is in the US)

INACTIVE INGREDIENT

Inactive ingredients water (aqua), potassium cocoate, hexylene glycol, sodium sulfate, tetrasodium edta, sodium lauryl sulfate, glycerin, sodium citrate, glyceryl oleate, fragrance, sodium glycolate, caprylyl/capryl glucoside, lauryl glucoside, magnesium nitrate, sodium hydroxide, methylchloroisothiazolinone, magnesium chloride, yellow 5, methylisothiazolinone, red 4

Questions? call 1 866 781 8787

Principal display panel and representative label

NDC 47593-503-59

ECOLAB

MEDI-STAT® Foam

Antimicrobial Hand Soap

Active Ingredient: Chloroxylenol 0.5%

Net Contents: 1250 mL (42.3 fl oz)

6000107

Ecolab · 1 Ecolab Place · St Paul MN 55102 USA

© 2022 Ecolab USA Inc · All rights reserved

Made in United States

755670/8502/0422